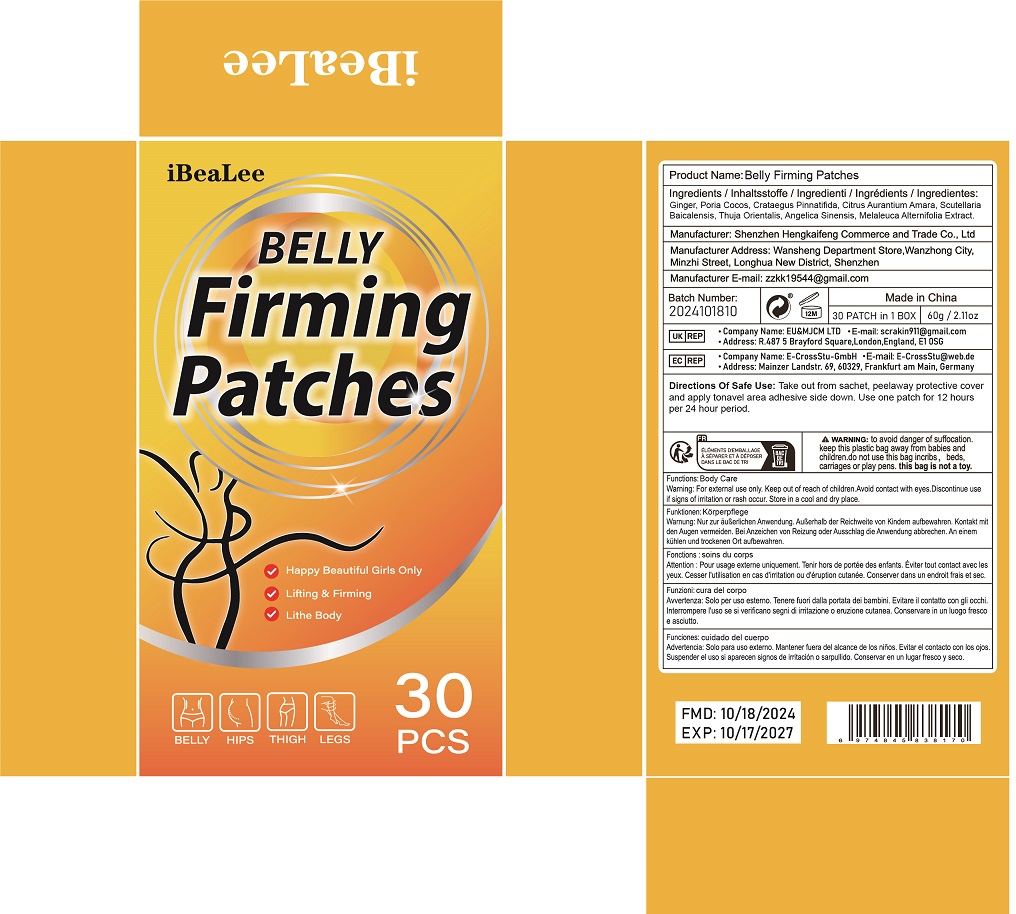 DRUG LABEL: Belly Firming Patches
NDC: 84117-033 | Form: PATCH
Manufacturer: Shenzhen Hengkaifeng Commerce and Trade Co., Ltd
Category: otc | Type: HUMAN OTC DRUG LABEL
Date: 20241017

ACTIVE INGREDIENTS: GINGER 1 g/100 1
INACTIVE INGREDIENTS: WATER

ACTIVE INGREDIENT

Ginger

Purpose

Nourish skin

Use

Abdominal patch

Warnings

For external use only,

Do not use this product if you have very sensitive skin

When using this product

Do not use this product if you have very sensitive skin

Keep Out Of Reach Of Children

this is not a toy

Directions Of Safe Use:

Cleanse skin thoroughly before appying.
Stick it on the belly

Other information

Keep tightly closed.Avoid storing at extreme temperatures (below 40° fand above 100° F).

Inactive ingredients

Poria Cocos, Crataegus Pinnatifida, Citrus Aurantium Amara, Scutellaria
Baicalensis, Thuja Orientalis, Angelica Sinensis, Melaleuca Alternifolia Extract.

Dosage and Administration

Stick it on the abdomen, 2-3 times a day